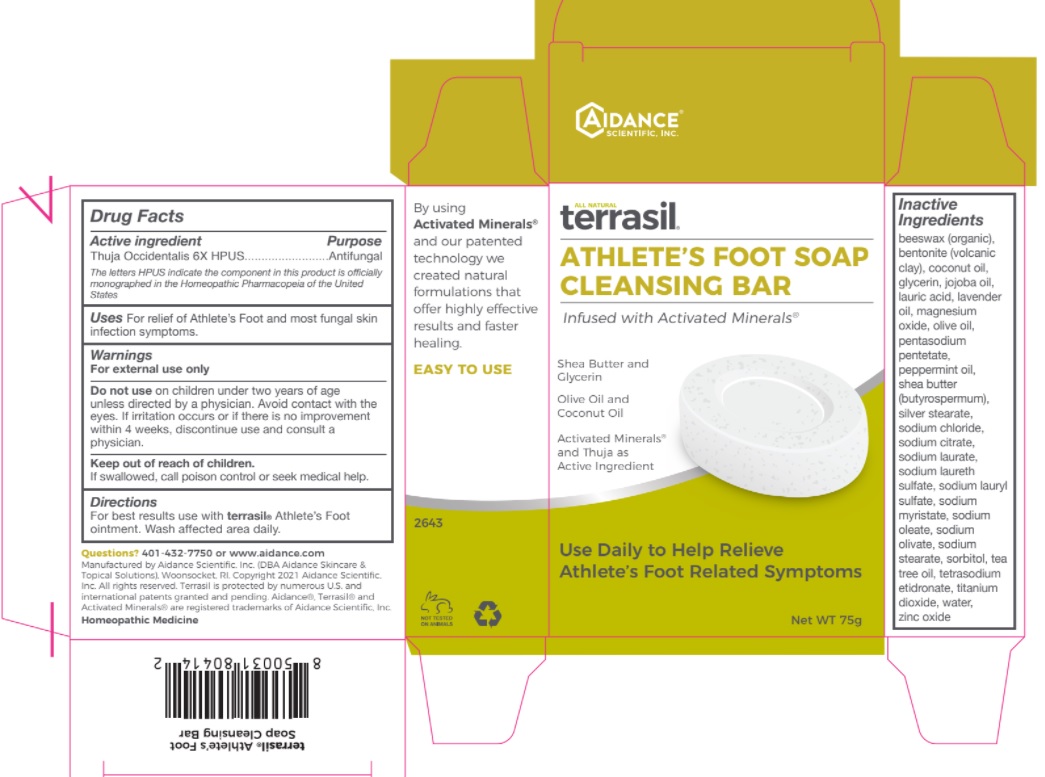 DRUG LABEL: TTerrasil Athletes Foot Cleansing Bar
NDC: 24909-210 | Form: SOAP
Manufacturer: Aidance Skincare & Topical Solutions, LLC
Category: homeopathic | Type: HUMAN OTC DRUG LABEL
Date: 20220525

ACTIVE INGREDIENTS: THUJA OCCIDENTALIS LEAF 6 [hp_X]/1 g
INACTIVE INGREDIENTS: YELLOW WAX; BENTONITE; COCONUT OIL; GLYCERIN; JOJOBA OIL; LAURIC ACID; LAVENDER OIL; MAGNESIUM OXIDE; OLIVE OIL; PENTASODIUM PENTETATE; PEPPERMINT OIL; SHEA BUTTER; SODIUM CHLORIDE; SODIUM CITRATE; SODIUM LAURATE; SODIUM LAURETH SULFATE; SODIUM LAURYL SULFATE; SODIUM MYRISTATE; SODIUM OLEATE; SODIUM STEARATE; SORBITOL; TEA TREE OIL; ETIDRONATE TETRASODIUM; TITANIUM DIOXIDE; WATER; ZINC OXIDE; SILVER OXIDE; STEARIC ACID; SODIUM OLIVATE

Drug Facts

Active Ingredient

Thuja Occidentalis 6X HPUS

Purpose

Antifungal

The letters HPUS indicate the component in this product is officially monographed in the Homeopathic Pharmacopeia of the United States

Uses

For relief of athlete's foot and most fungal skin infection symptoms.

Warnings

For external use only.

Do not use on children under two years of age, unless directed by a physician. Avoid contact with the eyes. If irritation occurs or if there is no improvement within 4 weeks, discontinue use and consult a physician.

Keep out of reach of children.

If swallowed, get medical help or contact a Poison Control Center right away.

Directions

For best results use with terrasil Athlete's Foot ointment. Wash affected area daily.

Inactive Ingredients

beeswax (organic), bentonite (volcanic clay), coconut oil, glycerin, jojoba oil, lauric acid, lavender oil, magnesium oxide, olive oil, pentasodium pentetate, peppermint oil, shea butter (butyrospermum), silver stearate, sodium chloride, sodium citrate, sodium laurate, sodium laureth sulfate, sodium lauryl sulfate, sodium myristate, sodium oleate, sodium olivate, sodium stearate, sorbitol, tea tree oil, tetrasodium etidronate, titanium dioxide, water, zinc oxide

Questions?

401-432-7750 or www.aidance.com